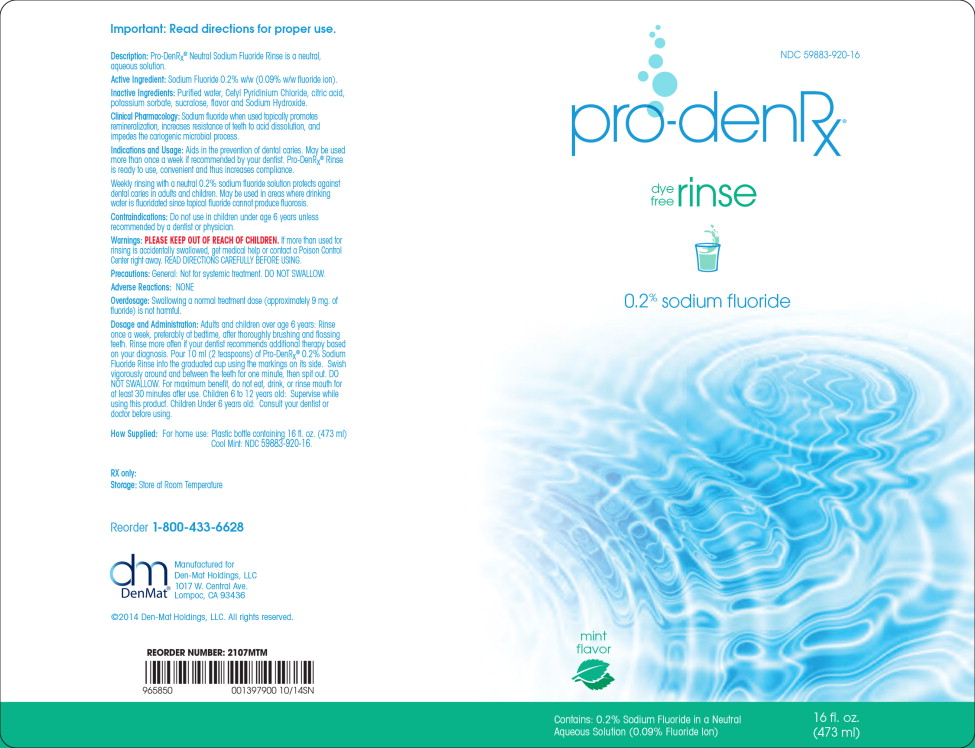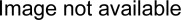 DRUG LABEL: Pro-Den Rx
NDC: 59883-920 | Form: RINSE
Manufacturer: Den-mat Holdings, Llc
Category: prescription | Type: HUMAN PRESCRIPTION DRUG LABEL
Date: 20190228

ACTIVE INGREDIENTS: SODIUM FLUORIDE 0.9 mg/1 mL
INACTIVE INGREDIENTS: WATER; CETYLPYRIDINIUM CHLORIDE; CITRIC ACID MONOHYDRATE; POTASSIUM SORBATE; SUCRALOSE; SODIUM HYDROXIDE

Description:

Pro-DenRx® Neutral Sodium Fluoride Rinse is a neutral, aqueous solution.

Active Ingredient:

Sodium Fluoride 0.2% w/w (0.09% w/w fluoride ion).

Inactive Ingredients:

Purified water, Cetyl Pyridinium Chloride, citric acid, potassium sorbate, sucralose, flavor and Sodium Hydroxide.

Clinical Pharmacology:

Sodium fluoride when used topically promotes remineralization, increases resistance of teeth to acid dissolution, and impedes the cariogenic microbial process.

Indications and Usage:

Aids in the prevention of dental caries. May be used more than once a week if recommended by your dentist. Pro-DenRx® Rinse is ready to use, convenient and thus increases compliance.

Weekly rinsing with a neutral 0.2% sodium fluoride solution protects against dental cares in adults and children. May be used in areas where drinking water is fluoridated since topical fluoride cannot produce fluorosis.

Contraindications:

Do not use in children under age 6 years unless recommended by a dentist or physician.

Warnings:

KEEP OUT OF REACH OF CHILDREN

PLEASE KEEP OUT OF REACH OF CHILDREN. If more than used for rinsing is accidentally swallowed, get medical help or contact a Poison Control Center right away. READ DIRECTIONS CAREFULLY BEFORE USING.

Precautions:

General: Not for systemic treatment. DO NOT SWALLOW.

Adverse Reactions:

NONE

Overdosage:

Swallowing a normal treatment dose (approximately 9 mg. of fluoride) is not harmful.

Dosage and Administration:

Adults and children over age 6 years: Rinse once a week, preferably at bedtime, after thoroughly brushing and flossing teeth. Rinse more often if your dentist recommends additional therapy based on your diagnosis. Pour 10 ml (2 teaspoons) of Pro-DenRx® 0.2% Sodium Fluoride Rinse into the graduated cup using the markings on its side. Swish vigorously around and between the teeth for one minute, then spit out. DO NOT SWALLOW. For maximum benefit, do not eat, drink, or rinse mouth for at least 30 minutes after use. Children 6 to 12 years old: Supervise while using this product. Children Under 6 years old: Consult your dentist or doctor before using.

How Supplied:

For home use: Plastic bottle containing 16 fl. oz. (473 ml) Cool Mint: NDC 59883-920-16.

RX only:

Storage: Store at Room Temperature

Reorder 1-800-433-6628
Manufactured for
Den-Mat Holdings, LLC 1017 W. Central Ave.
Lompoc, CA 93436

©2014 Den-Mat Holdings, LLC. All rights reserved.

Principal Display Panel - Bottle Label

NDC 59883-920-16

pro-denRx®

dye
free
rinse

0.2% sodium fluoride

mint
flavor

Contains: 0.2% Sodium Fluoride in a Neutral
Aqueous Solution (0.09% Fluoride Ion)

16 fl. oz.
(473 ml)